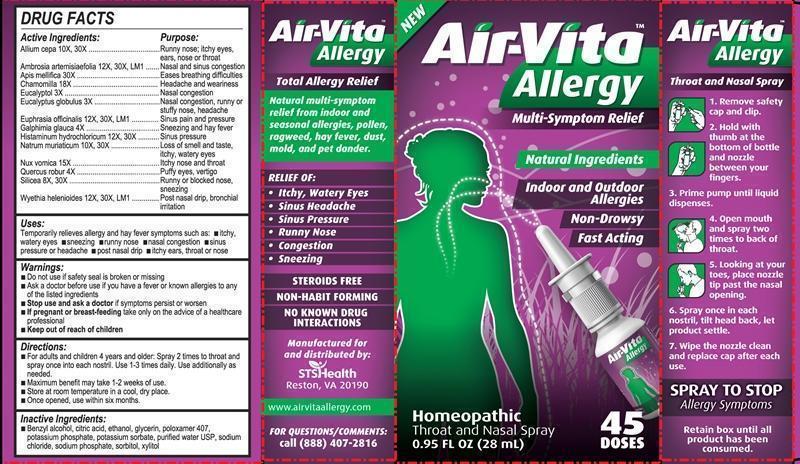 DRUG LABEL: Air-Vita Allergy
NDC: 54705-000 | Form: LIQUID
Manufacturer: Flutrends International Corporation
Category: homeopathic | Type: HUMAN OTC DRUG LABEL
Date: 20150109

ACTIVE INGREDIENTS: ONION 10 [hp_X]/28 mL; AMBROSIA ARTEMISIIFOLIA 12 [hp_X]/28 mL; APIS MELLIFERA 30 [hp_X]/28 mL; MATRICARIA RECUTITA 18 [hp_X]/28 mL; EUCALYPTOL 3 [hp_X]/28 mL; EUCALYPTUS GLOBULUS LEAF 3 [hp_X]/28 mL; EUPHRASIA STRICTA 12 [hp_X]/28 mL; GALPHIMIA GLAUCA FLOWERING TOP 4 [hp_X]/28 mL; HISTAMINE DIHYDROCHLORIDE 12 [hp_X]/28 mL; SODIUM CHLORIDE 10 [hp_X]/28 mL; STRYCHNOS NUX-VOMICA SEED 15 [hp_X]/28 mL; QUERCUS ROBUR TWIG BARK 4 [hp_X]/28 mL; SILICON DIOXIDE 8 [hp_X]/28 mL; WYETHIA HELENIOIDES ROOT 12 [hp_X]/28 mL
INACTIVE INGREDIENTS: BENZYL ALCOHOL; CITRIC ACID MONOHYDRATE; ALCOHOL; GLYCERIN; POLOXAMER 407; POTASSIUM PHOSPHATE, MONOBASIC; POTASSIUM SORBATE; WATER; SODIUM PHOSPHATE, DIBASIC, DIHYDRATE; SORBITOL; XYLITOL

Air-Vita Allergy

Drug Facts

____________________________________________________________________________________________________________________

HPUS active ingredients: Allium cepa, Ambrosia artemisiaefolia, Apis mellifica, Chamomilla, Eucalyptol, Eucalyptus globulus, Euphrasia officinalis, Galphimia glauca, Histaminum hydrochloricum, Natrum muriaticum, Nux vomica, Quercus robur, Silicea, Wyethia helenioides.

INDICATIONS AND USAGE

Uses: Temporarily relieves allergy and hay fever symptoms such as: •itchy, watery eyes •sneezing •runny nose •nasal congestion •sinus pressure or headache •post nasal drip •itchy ears, throat or nose

Natural multi-symptom relief from indoor and seasonal allergies, pollen, ragweed, hay fever, dust, mold, and pet dander.

Warnings

- Do not use if safety seal is broken or missing.
- Ask a doctor before use if you have a fever or known allergies to any of the listed ingredients.
- Stop use and ask your doctor if symptoms persist or worsen.
- If pregnant or breast-feeding, take only on advice of a healthcare professional.

- Keep out of reach of children.

Directions:

- For adults and children 4 years and older: Spray 2 times to throat and spray once into each nostril. Use 1-3 times daily. Use additionally as needed.
- Maximum benefit may take 1-2 weeks of use.
- Store at room temperature in a cool, dry place.
- Once opened, use within six months.

Throat and Nasal Spray

1. Remove safety cap and clip.
2. Hold with thumb at the bottom of bottle and nozzle between your fingers.
3. Prime pump until liquid dispenses.
4. Open mouth and spray two times to back of throat.
5. Looking at your toes, place nozzle tip past the nasal opening.
6. Spray once in each nostril, tilt head back, let product settle.
7. Wipe the nozzle clean and replace cap after each use.

INACTIVE INGREDIENT

Inactive Ingredients: Benzyl alcohol, citric acid, ethanol, glycerin, polozamer 407, potassium phosphate, potassium sorbate, purified water USP, sodium chloride, sodium phosphate, sorbitol, xylitol.

Drug Facts

____________________________________________________________________________________________________________________

HPUS active ingredients Purpose

Allium cepa 10X, 30X...................................Runny nose; itchy eyes, ears, nose or throat

Ambrosia artemisiaefolia 12X, 30X, LM1..................................Nasal and sinus congestion

Apis mellifica 30X.................................................................Eases breathing difficulties

Chamomilla 18X......................................................................Headache and weariness

Eucalyptol 3X.....................................................................................Nasal congestion

Eucalyptus globulus 3X...........................Nasal congestion, runny or stuffy nose, headache

Euphrasia officinalis 12X, 30X, LM1.............................................Sinus pain and pressure

Galphimia glauca 4X..................................................................Sneezing and hay fever

Histaminum hydrochloricum 12X, 30X......................................................Sinus pressure

Natrum muriaticum 10X, 30X............................Loss of smell and taste, itchy, watery eyes

Nux vomica 15X...........................................................................Itchy nose and throat

Quercus robur 4X.............................................................................Puffy eyes, vertigo

Silicea 8X, 30X.............................................................Runny or blocked nose, sneezing

Wyethia helenioides 12X, 30X, LM1...............................Post nasal drip, bronchial irritation